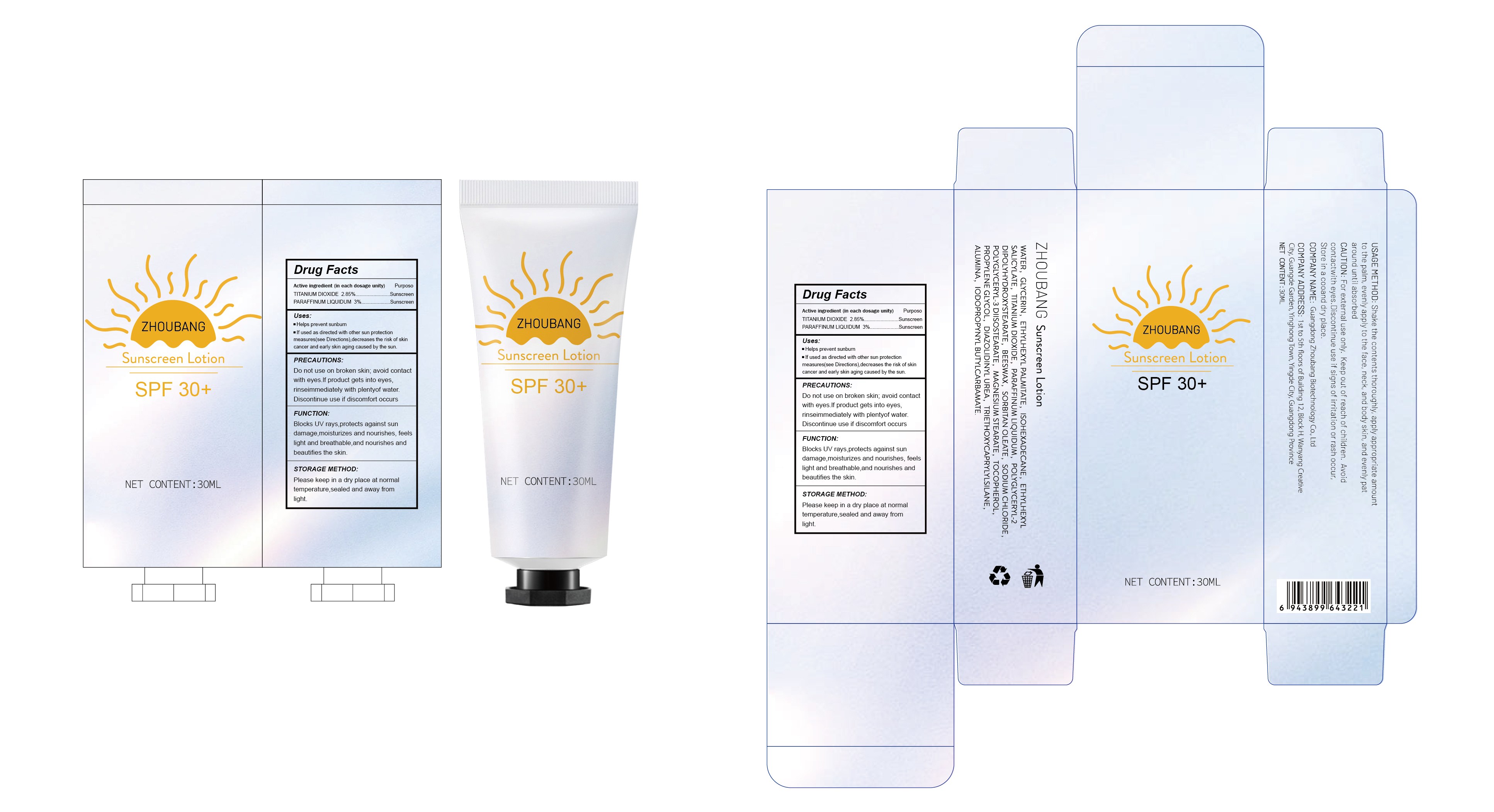 DRUG LABEL: sunscreen
NDC: 87357-001 | Form: LOTION
Manufacturer: Guangdong Zhoubang Biotechnology Co., Ltd
Category: otc | Type: HUMAN OTC DRUG LABEL
Date: 20260121

ACTIVE INGREDIENTS: TITANIUM DIOXIDE 2.85 g/100 mL; ETHYLHEXYL SALICYLATE 3 g/100 mL
INACTIVE INGREDIENTS: IODOPROPYNYL BUTYLCARBAMATE; SODIUM CHLORIDE; SORBITAN OLEATE; WATER; ISOHEXADECANE; ETHYLHEXYL PALMITATE; POLYGLYCERYL-3 DIISOSTEARATE; MAGNESIUM STEARATE; ALUMINA; DIAZOLIDINYL UREA; PARAFFINUM LIQUIDUM; POLYGLYCERYL-2 DIPOLYHYDROXYSTEARATE; TOCOPHEROL; GLYCERIN; PROPYLENE GLYCOL; TRIETHOXYCAPRYLYLSILANE; BEESWAX

INACTIVE INGREDIENT

WATER
GLYCERIN
ETHYLHEXYL PALMITATE
ISOHEXADECANE
PARAFFINUM LIQUIDUM
POLYGLYCERYL-2 DIPOLYHYDROXYSTEARATE
BEESWAX
SORBITAN OLEATE
SODIUM CHLORIDE
POLYGLYCERYL-3 DIISOSTEARATE
MAGNESIUM STEARATE
TOCOPHEROL
PROPYLENE GLYCOL
DIAZOLIDINYL UREA
TRIETHOXYCAPRYLYLSILANE
ALUMINA
IODOPROPYNYL BUTYLCARBAMATE

DOSAGE AND ADMINISTRATION

Shake the contents thoroughly, apply appropriate amount to the palm, evenly apply to the face, neck, and body skin, and evenly pat
around until absorbed

WARNINGS

For external use only. Keep out of reach of children. Avoid contactwith eyes.Discontinue use if signs of irritation or rash occur,
Store in a cooand dry place.

ACTIVE INGREDIENT

TITANIUM DIOXIDE 2.85%
ETHYLHEXYL SALICYLATE 3%

Do not use on broken skin; avoid contact with eyes.lf product gets into eyes, rinseimmediately with plentyof water.Discontinue use if discomfort occurs

PURPOSE

Sun protection

INDICATIONS AND USAGE

Helps prevent sunburn
If used as directed with other sun protection measures(see Directions),decreases the risk of skin cancer and early skin aging caused by the sun.